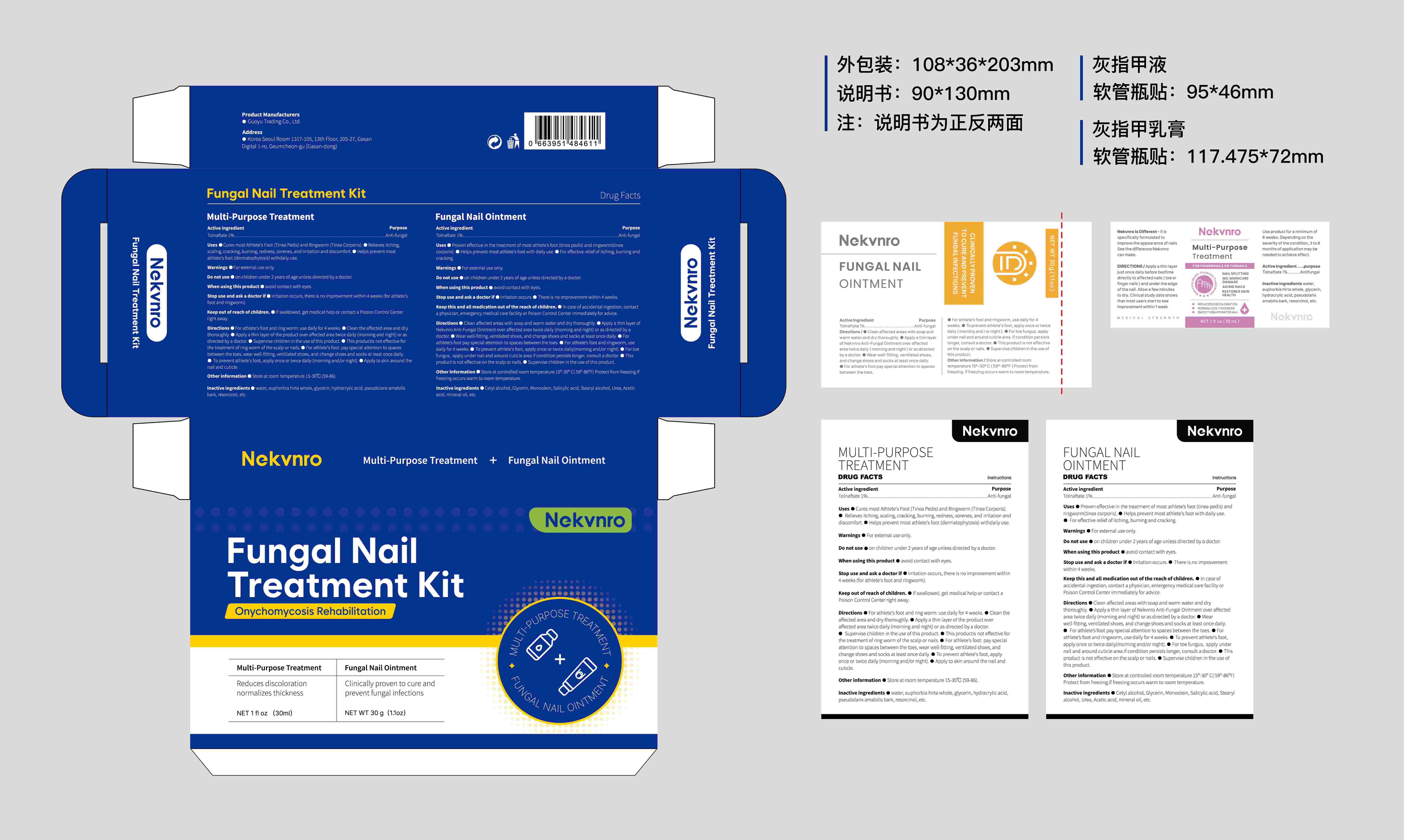 DRUG LABEL: Nekvnro Fungal Nail Treatment Kit Fungal Nail Ointment.
NDC: 84844-016 | Form: PASTE
Manufacturer: Guoyu Trading Co., Ltd.
Category: otc | Type: HUMAN OTC DRUG LABEL
Date: 20241121

ACTIVE INGREDIENTS: TOLNAFTATE 1 g/100 g
INACTIVE INGREDIENTS: GLYCERIN; STEARYL ALCOHOL; ACETIC ACID; MINERAL OIL; UREA; CETYL ALCOHOL; SALICYLIC ACID; GLYCERYL MONOOLEATE

84844-016 017

Active Ingredient

30G:

Tolnaftate 1%

50ML:

Tolnaftate 1%

Purpose

Anti-fungal

Use

■Proven effective in the treatment of most athlete’s foot (tinea pedis) and ringworm(tinea corporis).
■Helps prevent most athlete's foot with daily use.

■For effective relief of itching, burning and cracking.

Warnings

For external use only.

Do not use

on children under 2 years of age unless directed by a doctor.

When Using

this product avoid contact with eyes.

Stop Use

and ask a doctor if
■Irritation occurs.

■There is no improvement within 4 weeks.

Ask Doctor

■Irritation occurs.

■There is no improvement within 4 weeks.

Keep Oot Of Reach Of Children

In case of accidental ingestion, contact a physician, emergency medical care facility or Poison Control Center immediately for advice.

Directions

■Clean affected areas with soap and warm water and dry thoroughly.

■Apply a thin layer of Nekvnro Anti-Fungal Ointment over affected area twice daily (morning and night) or as directed by a doctor.

■ Wear well-fitting, ventilated shoes, and change shoes and socks at least once daily.

■ For athlete’s foot pay special attention to spaces between the toes.

■For athlete’s foot and ringworm, use daily for 4 weeks.

■To prevent athlete's foot, apply once or twice daily(morning and/or night).

■For toe fungus, apply under nail and around cuticle area.If condition persists longer, consult a doctor.

■ This product is not effective on the scalp or nails.

■Supervise children in the use of this product.

Other information

Store at controlled room temperature 15º-30º C(59º-86ºF) Protect from freezing.If freezing occurs warm to room temperature.

Inactive ingredients

30G:

Cetyl alcohol, Glycerin, Monoolein, Salicylic acid,Stearyl alcohol, Urea, Acetic acid，mineral oil，etc.

30ML:

water, euphorbia hirta whole, glycerin, hydracrylic acid, pseudolarix amabilis bark, resorcinol